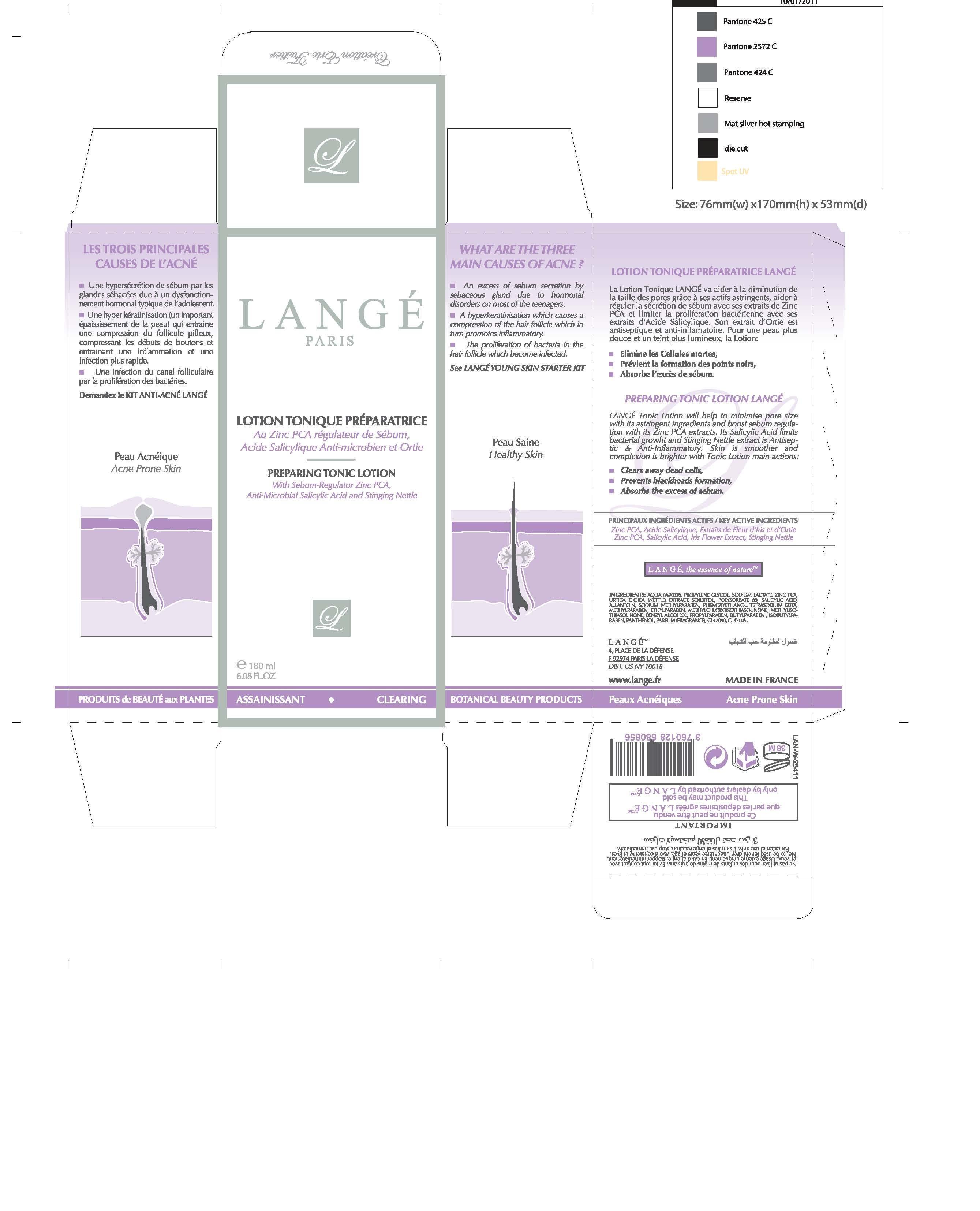 DRUG LABEL: Preparing Tonic
NDC: 51830-054 | Form: LOTION
Manufacturer: Lange SAS
Category: otc | Type: HUMAN OTC DRUG LABEL
Date: 20130212

ACTIVE INGREDIENTS: SALICYLIC ACID 1.8 mg/180 mg
INACTIVE INGREDIENTS: WATER; PROPYLENE GLYCOL; SORBITOL; PHENOXYETHANOL; METHYLPARABEN; ETHYLPARABEN; PROPYLPARABEN; BUTYLPARABEN; ISOBUTYLPARABEN; SODIUM LACTATE; POLYSORBATE 80; BENZYL ALCOHOL; METHYLCHLOROISOTHIAZOLINONE; METHYLISOTHIAZOLINONE; TRIETHYLENE GLYCOL; PROPYLENE GLYCOL; MAGNESIUM NITRATE; MAGNESIUM CHLORIDE; EDETATE SODIUM; METHYLPARABEN SODIUM; PANTHENOL; ALLANTOIN; FD&C YELLOW NO. 5; IMIDUREA; CITRIC ACID MONOHYDRATE; ZINC PIDOLATE; ALCOHOL; URTICA DIOICA LEAF

KEY ACTIVE INGREDIENTS
Zinc PCA, Salicyclic Acid, Iris Flower Extract, Stinging Nettle

PURPOSE

PREPARING TONIC LOTION
With Sebum-Regulator Zinc PCA,
Anti-Microbial Salicylic Acid and Stinging Nettle

Keep out of reach of children.

INDICATIONS AND USAGE

PREPARING TONIC LOTION LANGE
LANGE Tonic Lotion will help to minimise pore size with its astringent ingredients and boost sebum regulation with its Zinc PCA extracts. Its Salicylic Acid limits bacterial growht and Stinging Nettle extract is antiseptic and Anti-Inflammatory. Skin is smoother and complexion is brighter with Tonic Lotion main actions:
Clears away dead cells,
Prevents blackheads formation,
Absorbs the excess of sebum.

WARNINGS

Not to be used for children under three years of age. Avoid contact with Eyes.
For external use only. If skin has allergic reaction, stop use immediately.

DOSAGE AND ADMINISTRATION

180 ml
6.08 FL. OZ

INACTIVE INGREDIENT

WATER
PROPYLENE GLYCOL
URTICA DIOICA EXTRACT
SORBITOL
PHENOXYETHANOL
METHYLPARABEN
ETHYLPARABEN
BUTYLPARABEN
PROPYLPARABEN
ISOBUTYLPARABEN
SODIUM LACTATE
ZINC PCA
POLYSORBATE 80
BENZYL ALCOHOL
METHYLCHLOROISOTHIAZOLINONE
METHYLISOTHIAZOLINONE
TRIETHYLENE GLYCOL
MAGNESIUM NITRATE
MAGNESIUM CHLORIDE
TETRASODIUM EDTA
SALICYLIC ACID
PANTHENOL
ALLANTOIN
YELLOW FIVE
ALCOHOL DENAT.
IMIDAZOLIDINYL UREA
CITRIC ACID